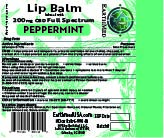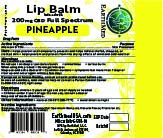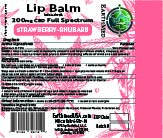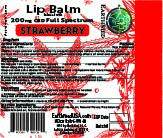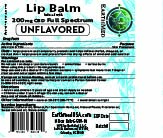 DRUG LABEL: Earthmed Lip Balm Pineapple
NDC: 82876-988 | Form: SALVE
Manufacturer: Earthmed LLC
Category: otc | Type: HUMAN OTC DRUG LABEL
Date: 20250805

ACTIVE INGREDIENTS: ALLANTOIN 0.045 g/4.455 g
INACTIVE INGREDIENTS: COCONUT OIL 1.23 g/4.455 g; REBAUDIOSIDE A 0.075 g/4.455 g; ALCOHOL 0.075 g/4.455 g; PEG-8 BEESWAX 0.85 g/4.455 g; ALMOND OIL 0.9 g/4.455 g; RICE BRAN OIL 0.9 g/4.455 g; CANNABIDIOL 0.21 g/4.455 g

Earthmed Lip balm

Active Ingredients

Allantoin 1% .................................................................................................. Skin Protectant

Purpose

Allantoin 0.72% .................................................................................................. Skin Protectant

Uses

helps prevent and temporarily protects and helps relieve chafed, chapped, or
cracked skin • helps prevent and protect from the drying effects of wind and cold weather

Warnings

FOR EXTERNAL USE ONLY.

When using this product

Do not get into eyes

DO NOT USE

on deep or puncture wounds • animal bites • serious burns

Stop use and ask a doctor if

The condition worsens, symptoms last more than 7 days, the condition clears but occurs again within a few days.

Stop use and ask a doctor if

Condition worsens, Symptoms last more than 7 days, Condition clears up but occurs again within a few days.

If pregnant or breastfeeding

Consult a health professional before use

In case of an overdose

seek medical help or contact a poison control center right away

Directions

• Adults and children 2 years of age and older: Apply as needed
• Children under 2 years of age: Do not use, consult a doctor

Keep out of reach of children

Keep out of reach of children

Other information

Store at 68-77 degrees F, Avoid direct sunlight

Inactive ingredients

Beeswax, Coconut oil, Ethanol, Full Spectrum Hemp oil, Natural Flavor, Sweet Almond oil,
Rice bran oil, Stevia extract